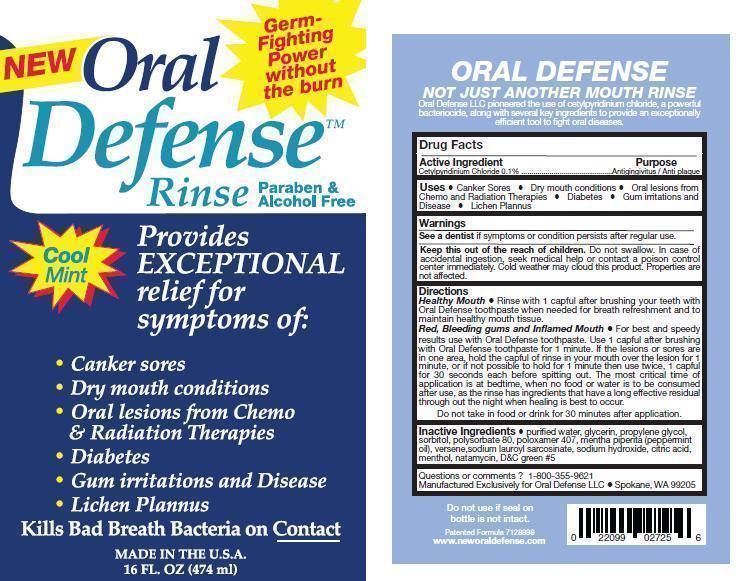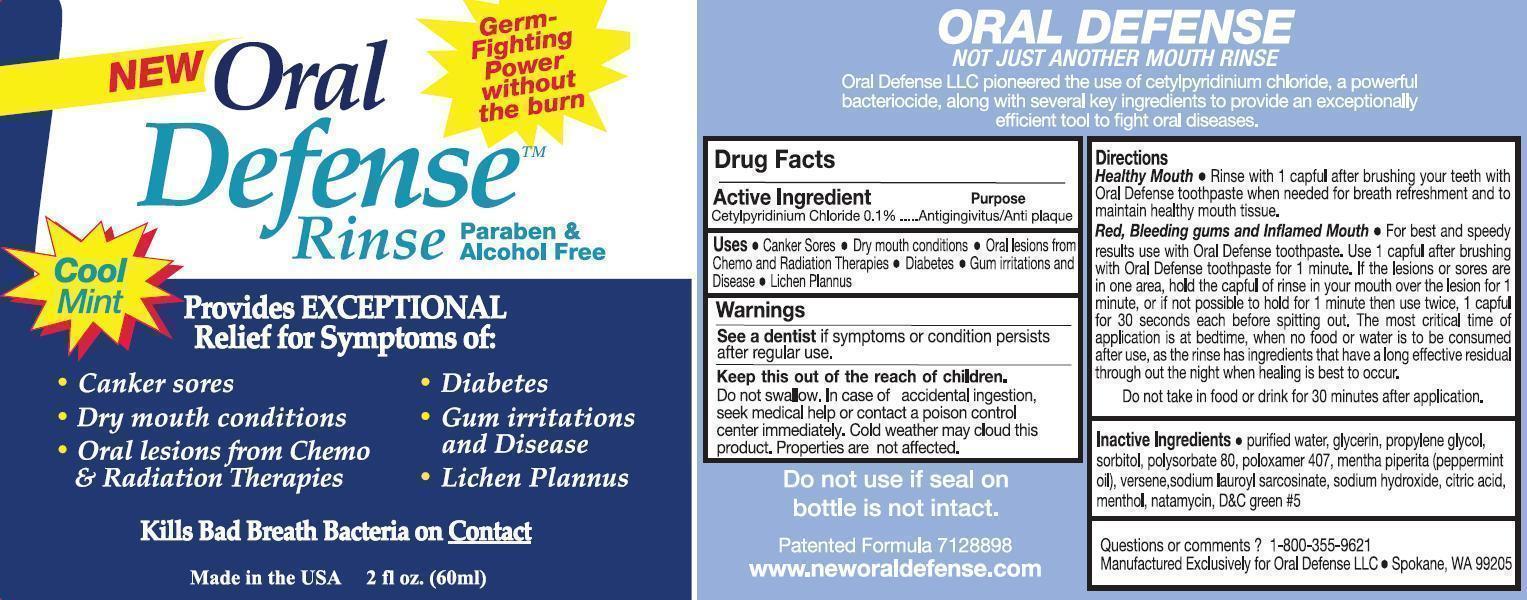 DRUG LABEL: Oral Defense
NDC: 52644-001 | Form: MOUTHWASH
Manufacturer: Oral Defense, LLC
Category: otc | Type: HUMAN OTC DRUG LABEL
Date: 20120518

ACTIVE INGREDIENTS: CETYLPYRIDINIUM CHLORIDE .47 mL/474 mL
INACTIVE INGREDIENTS: WATER; EDETATE DISODIUM; POLOXAMER 407; PROPYLENE GLYCOL; SORBITOL; SACCHARIN SODIUM; GLYCERIN; POLYSORBATE 80; NATAMYCIN; SODIUM LAUROYL SARCOSINATE; PEPPERMINT OIL; MENTHOL; SODIUM HYDROXIDE; CITRIC ACID MONOHYDRATE

Oral Defense Mouth Rinse

Drug Facts

Active Ingredients

Cetylpyridinium Chloride 0.1%

Pupose

Antigingivitus/Anti-Plaque

Uses

- Canker sores

- Dry mouth conditions

- Oral lesions from chemo and radiation therapies

- Diabetes

- Gum irritations and disease

- Lichen Plannus

Warnings

See a dentist if symptoms or conditions persist after regular use.

Keep out of the reach of children

Do not swallow. In case of accidental ingestion, seek medical help or contact a poison control center immediately. Cold weather may cloud this product. Properties are not affected.

Directions

Healthy Mouth

Rinse with 1 capful after brushing your teeth with Oral Defense toothpaste when needed for breath refreshment and to maintain healthy mouth tissue.

Red, Bleeding gums and inflamed mouth

For best and speedy results use with Oral Defense toothpaste. Use 1 capful after brushing with Oral Defense Toothpaste for 1 minute. If the lesions or sores re in one area, hold the capful of rinse in your mouth over the lesion for 1 minute, or if not possible to hold for 1 minute then use twice, 1 capful for 30 seconds each before spitting out. The most critical time of application is at bedtime, when no food or water is to be consumed after use, as the rinse has ingredients that have a long effective residual throughout the night when healing is best to occur.

Inactive Ingredients

purified water, glycerin, propylene glycol, sorbitol, polysorbate 80, poloxamer 407, mentha piperita (peppermint oil), versene, sodium lauroyl sarcosinate, sodium hydroxide, citric acid, menthol, natamycin, FD and C green #5

Questions or comments

1-800-355-9621

Manufactured Exclusively for Oral Defense, LLC Spokane, WA 99205